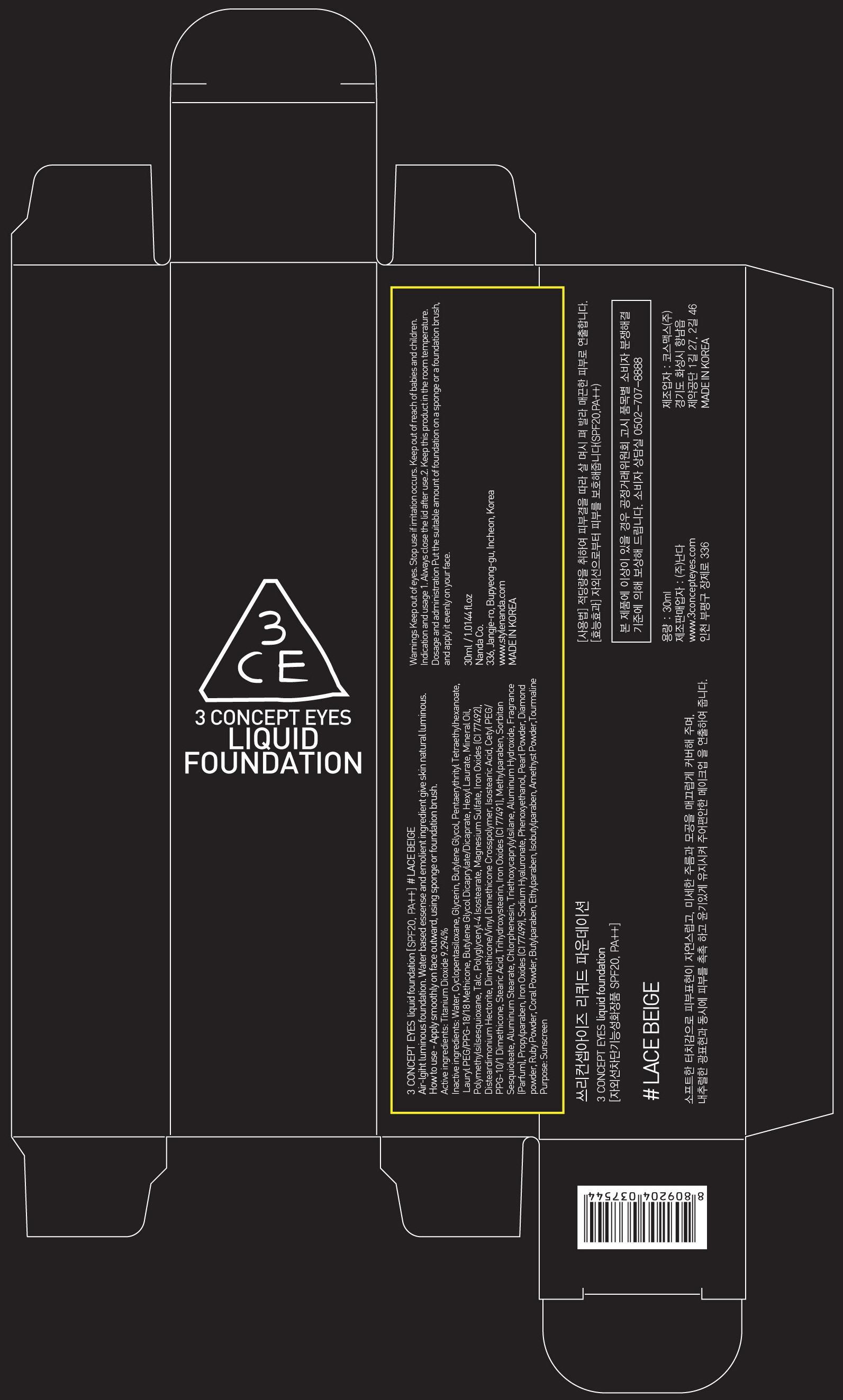 DRUG LABEL: 3 CONCEPT EYES LIQUID FOUNDATION LACE BEIGE
NDC: 60764-008 | Form: CREAM
Manufacturer: NANDA CO., LTD.
Category: otc | Type: HUMAN OTC DRUG LABEL
Date: 20131003

ACTIVE INGREDIENTS: Titanium Dioxide 2.78 mg/30 mL
INACTIVE INGREDIENTS: Water; Butylene Glycol

ACTIVE INGREDIENT

Active ingredients: Titanium Dioxide 9.294%

INACTIVE INGREDIENT

Inactive ingredients: Water, Cyclopentasiloxane, Glycerin, Butylene Glycol, Pentaerythrityl Tetraethylhexanoate, Lauryl PEG/PPG-18/18 Methicone, Butylene Glycol Dicaprylate/Dicaprate, Hexyl Laurate, Mineral Oil, Polymethylsilsesquioxane, Talc, Polyglyceryl-4 Isostearate, Magnesium Sulfate, Iron Oxides (CI 77492), Disteardimonium Hectorite, Dimethicone/Vinyl Dimethicone Crosspolymer, Isostearic Acid, Cetyl PEG/PPG-10/1 Dimethicone, Stearic Acid, Trihydroxystearin, Iron Oxides (CI 77491), Methylparaben, Sorbitan Sesquioleate, Aluminum Stearate, Chlorphenesin, Triethoxycaprylylsilane, Aluminum Hydroxide, Fragrance(Parfum), Propylparaben, Iron Oxides (CI 77499), Sodium Hyaluronate, Phenoxyethanol, Pearl Powder, Diamond powder, Ruby Powder, Coral Powder, Butylparaben, Ethylparaben, Isobutylparaben, Amethyst Powder,Tourmaline

PURPOSE

Purpose: Sunscreen

WARNINGS

Warnings Keep out of eyes. Stop use if irritation occurs. Keep out of reach of babies and children.

KEEP OUT OF REACH OF CHILDREN

Keep out of reach of babies and children.

INDICATIONS AND USAGE

Indication and usage 1. Always close the lid after use.2. Keep this product in the room temperature.

Dosage and administration Put the suitable amount of foundation on a sponge or a foundation brush, and apply it evenly on your face.